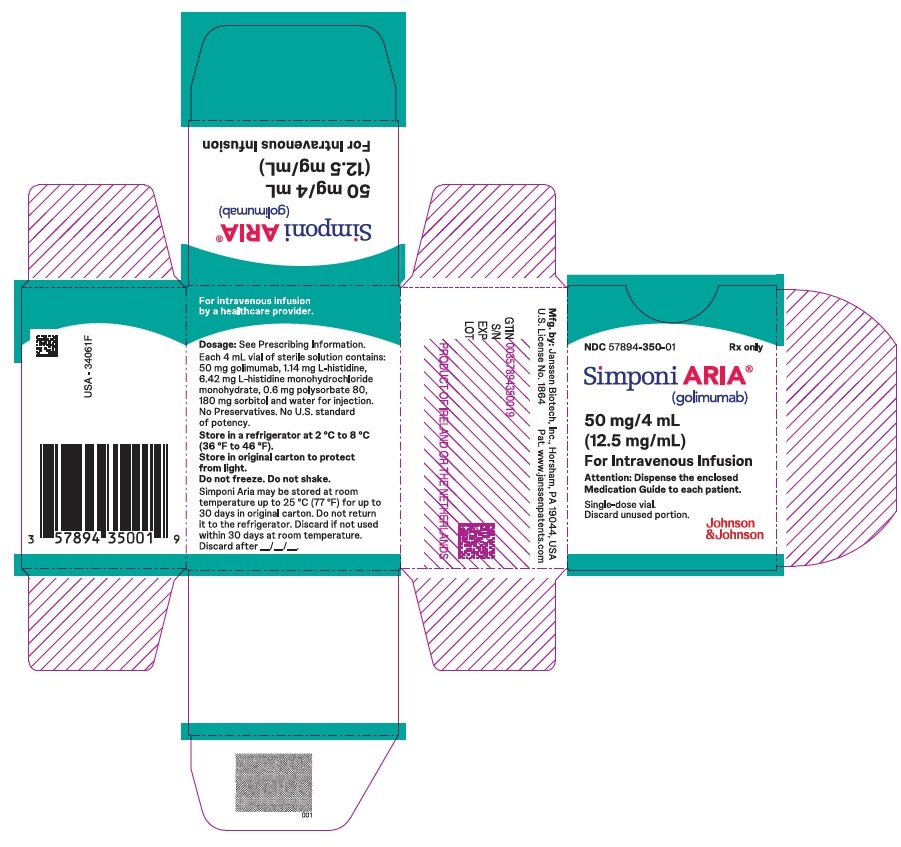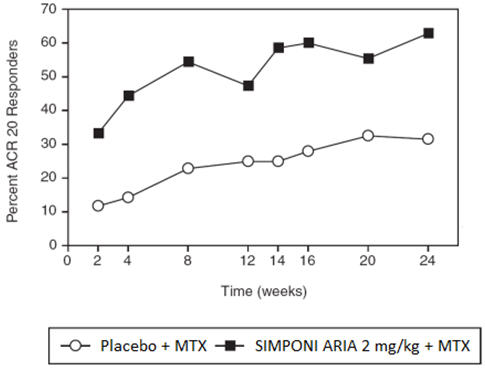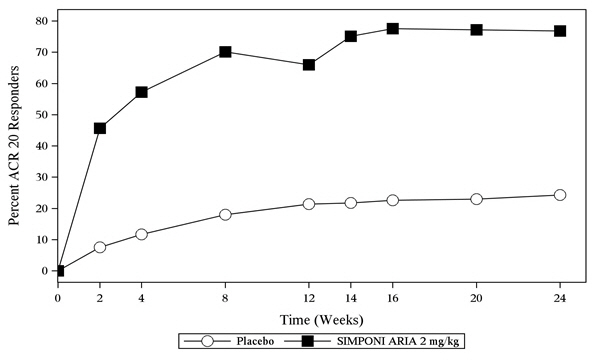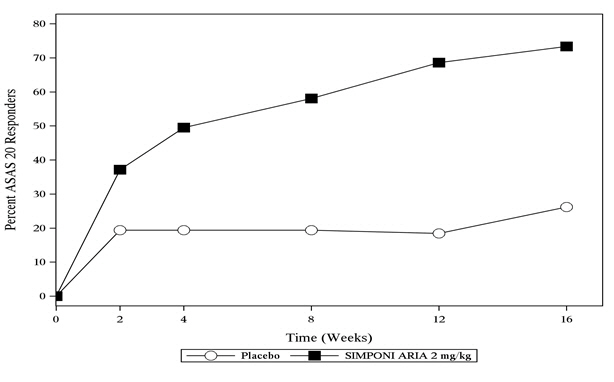 DRUG LABEL: SIMPONI ARIA
NDC: 57894-350 | Form: SOLUTION
Manufacturer: Janssen Biotech, Inc.
Category: prescription | Type: HUMAN PRESCRIPTION DRUG LABEL
Date: 20250909

ACTIVE INGREDIENTS: GOLIMUMAB 50 mg/4 mL
INACTIVE INGREDIENTS: HISTIDINE MONOHYDROCHLORIDE MONOHYDRATE 6.42 mg/4 mL; HISTIDINE 1.14 mg/4 mL; POLYSORBATE 80 0.6 mg/4 mL; WATER; SORBITOL 180 mg/4 mL

HIGHLIGHTS OF PRESCRIBING INFORMATION

These highlights do not include all the information needed to use SIMPONI ARIA safely and effectively. See full prescribing information for SIMPONI ARIA.
SIMPONI ARIA®(golimumab) injection, for intravenous use
Initial U.S. Approval: 2009

WARNING: SERIOUS INFECTIONS and MALIGNANCY

See full prescribing information for complete boxed warning.

- Serious infections leading to hospitalization or death including tuberculosis (TB), bacterial sepsis, invasive fungal (such as histoplasmosis), and other opportunistic infections have occurred in patients receiving SIMPONI ARIA (5.1).
- Discontinue SIMPONI ARIA if a patient develops a serious infection or sepsis (5.1).
- Perform test for latent TB; if positive, start treatment for TB prior to starting SIMPONI ARIA (5.1).
- Monitor all patients for active TB during treatment, even if initial latent TB test is negative (5.1).
- Lymphoma and other malignancies, some fatal, have been reported in children and adolescent patients treated with TNF blockers, of which SIMPONI ARIA is a member (5.2).

1 INDICATIONS AND USAGE

SIMPONI ARIA is a tumor necrosis factor (TNF) blocker indicated for the treatment of:

- Adult patients with moderately to severely active Rheumatoid Arthritis (RA) in combination with methotrexate (1.1)
- Active Psoriatic Arthritis (PsA) in patients 2 years of age and older (1.2)
- Adult patients with active Ankylosing Spondylitis (AS) (1.3)
- Active polyarticular Juvenile Idiopathic Arthritis (pJIA) in patients 2 years of age and older (1.4)

2 DOSAGE AND ADMINISTRATION

- Adult patients with Rheumatoid Arthritis, Psoriatic Arthritis, and Ankylosing Spondylitis:
  - 2 mg/kg intravenous infusion over 30 minutes at weeks 0 and 4, and every 8 weeks thereafter (2.1)
- Pediatric patients with polyarticular Juvenile Idiopathic Arthritis and Psoriatic Arthritis:
  - 80 mg/m^2intravenous infusion over 30 minutes at weeks 0 and 4, and every 8 weeks thereafter (2.2)
- Dilution of supplied SIMPONI ARIA solution with 0.9% Sodium Chloride Injection, USP is required prior to administration. Alternatively, 0.45% Sodium Chloride Injection, USP can also be used (2.4)

3 DOSAGE FORMS AND STRENGTHS

- Injection: 50 mg/4 mL (12.5 mg/mL) solution in a single-dose vial (3)

4 CONTRAINDICATIONS

- None (4)

5 WARNINGS AND PRECAUTIONS

- Serious Infections: Do not start SIMPONI ARIA during an active infection. If an infection develops, monitor carefully, and stop SIMPONI ARIA if infection becomes serious (5.1).
- Invasive Fungal Infections: For patients who develop a systemic illness on SIMPONI ARIA, consider empiric antifungal therapy for those who reside in or travel to regions where mycoses are endemic (5.1).
- Hepatitis B Reactivation: Monitor HBV carriers during and several months after therapy. If reactivation occurs, stop SIMPONI ARIA and begin anti-viral therapy (5.1).
- Malignancies: More cases of lymphoma have been observed among patients receiving TNF blockers compared with patients in the control groups. Cases of other malignancies have been observed among patients receiving TNF blockers (5.2).
- Congestive Heart Failure: Worsening, or new onset, may occur. Stop SIMPONI ARIA if new or worsening symptoms occur (5.3).
- Demyelinating Disorders: Exacerbation or new onset may occur (5.4).
- Lupus-like Syndrome: Discontinue SIMPONI ARIA if symptoms develop (5.5).
- Hypersensitivity Reactions: Serious systemic hypersensitivity reactions including anaphylaxis may occur (5.11).

6 ADVERSE REACTIONS

Most common adverse reactions (incidence ≥ 3%) are: upper respiratory tract infection, alanine aminotransferase increased, viral infection, aspartate aminotransferase increased, neutrophil count decreased, bronchitis, hypertension, and rash (6.1).

To report SUSPECTED ADVERSE REACTIONS, contact Janssen Biotech, Inc. at 1-800-JANSSEN (1-800-526-7736) or FDA at 1-800-FDA-1088 or www.fda.gov/medwatch.

7 DRUG INTERACTIONS

- Biologics, including abatacept and anakinra: Increased risk of serious infections (5.1, 5.6, 5.7, 5.8, 7.2).
- Live vaccines should not be given with SIMPONI ARIA (5.10, 7.3).

FULL PRESCRIBING INFORMATION

WARNING: SERIOUS INFECTIONS and MALIGNANCY

SERIOUS INFECTIONS

Patients treated with SIMPONI ARIA are at increased risk for developing serious infections that may lead to hospitalization or death [see Warnings and Precautions (5.1)] . Most patients who developed these infections were taking concomitant immunosuppressants such as methotrexate or corticosteroids.

Discontinue SIMPONI ARIA if a patient develops a serious infection.

Reported infections with TNF blockers, of which SIMPONI ARIA is a member, include:

- Active tuberculosis, including reactivation of latent tuberculosis. Patients with tuberculosis have frequently presented with disseminated or extrapulmonary disease. Test patients for latent tuberculosis before SIMPONI ARIA use and during therapy. Initiate treatment for latent tuberculosis prior to SIMPONI ARIA use.
- Invasive fungal infections including histoplasmosis, coccidioidomycosis, candidiasis, aspergillosis, blastomycosis and pneumocystosis. Patients with histoplasmosis or other invasive fungal infections may present with disseminated, rather than localized, disease. Antigen and antibody testing for histoplasmosis may be negative in some patients with active infection. Consider empiric antifungal therapy in patients at risk for invasive fungal infections who develop severe systemic illness.
- Bacterial, viral, and other infections due to opportunistic pathogens, including Legionella and Listeria.

Consider the risks and benefits of treatment with SIMPONI ARIA prior to initiating therapy in patients with chronic or recurrent infection.

Monitor patients closely for the development of signs and symptoms of infection during and after treatment with SIMPONI ARIA, including the possible development of tuberculosis in patients who tested negative for latent tuberculosis infection prior to initiating therapy [see Warnings and Precautions (5.1)] .

MALIGNANCY

Lymphoma and other malignancies, some fatal, have been reported in children and adolescent patients treated with TNF-blockers, of which SIMPONI ARIA is a member [see Warnings and Precautions (5.2)] .

1 INDICATIONS AND USAGE

1.1 Rheumatoid Arthritis (RA)

SIMPONI ARIA, in combination with methotrexate (MTX), is indicated for the treatment of adult patients with moderately to severely active rheumatoid arthritis.

1.2 Psoriatic Arthritis (PsA)

SIMPONI ARIA is indicated for the treatment of active psoriatic arthritis in patients 2 years of age and older.

1.3 Ankylosing Spondylitis (AS)

SIMPONI ARIA is indicated for the treatment of adult patients with active ankylosing spondylitis.

1.4 Polyarticular Juvenile Idiopathic Arthritis (pJIA)

SIMPONI ARIA is indicated for the treatment of active polyarticular juvenile idiopathic arthritis (pJIA) in patients 2 years of age and older.

2 DOSAGE AND ADMINISTRATION

2.1 Dosage in Adults with Rheumatoid Arthritis, Psoriatic Arthritis, and Ankylosing Spondylitis

The SIMPONI ARIA dosage regimen is 2 mg per kg given as an intravenous infusion over 30 minutes at weeks 0 and 4, and every 8 weeks thereafter. Follow the dilution and administration instructions for SIMPONI ARIA [see Dosage and Administration (2.4)] .

For patients with rheumatoid arthritis (RA), SIMPONI ARIA should be given in combination with methotrexate.

The efficacy and safety of switching between intravenous and subcutaneous formulations and routes of administration have not been established.

2.2 Dosage in Pediatric Patients with Polyarticular Juvenile Idiopathic Arthritis and Psoriatic Arthritis

The SIMPONI ARIA dosage regimen, based on body surface area (BSA), is 80 mg/m^2given as an intravenous infusion over 30 minutes at weeks 0 and 4, and every 8 weeks thereafter. Follow the dilution and administration instructions for SIMPONI ARIA [see Dosage and Administration (2.4)] .

2.3 Evaluation for Tuberculosis and Hepatitis B Prior to Dosage

Prior to initiating SIMPONI ARIA and periodically during therapy, evaluate patients for active tuberculosis and test for latent infection [see Warnings and Precautions (5.1)] . Prior to initiating SIMPONI ARIA, test patients for hepatitis B viral infection [see Warnings and Precautions (5.1)] .

2.4 Important Administration Instructions

SIMPONI ARIA solution for intravenous infusion should be diluted by a healthcare professional using aseptic technique as follows:

1. Calculate the dosage and the number of SIMPONI ARIA vials needed based on the recommended adult dosage of 2 mg/kg and the patient's weight for RA, PsA and AS. Calculate the dosage and number of SIMPONI ARIA vials needed based on the recommended pediatric dosage of 80 mg/m^2and the patient's body surface area (BSA), for pJIA and pediatric patients with PsA. Each 4 mL vial of SIMPONI ARIA contains 50 mg of golimumab.
2. Check that the solution in each vial is colorless to light yellow. The solution may develop a few fine translucent particles, as golimumab is a protein. Do not use if opaque particles, discoloration, or other foreign particles are present.
3. Dilute the total volume of the SIMPONI ARIA solution with 0.9% Sodium Chloride Injection, USP to a final volume of 100 mL. For example, this can be accomplished by withdrawing a volume of the 0.9% Sodium Chloride Injection, USP from the 100-mL infusion bag or bottle equal to the total volume of SIMPONI ARIA. Slowly add the total volume of SIMPONI ARIA solution to the 100-mL infusion bag or bottle. Gently mix. Discard any unused solution remaining in the vials. Alternatively, SIMPONI ARIA can be diluted using the same method described above with 0.45% Sodium Chloride Injection, USP.
4. Prior to infusion, visually inspect the diluted SIMPONI ARIA solution for particulate matter or discoloration. Do not use if these are present.
5. Use only an infusion set with an in-line, sterile, non-pyrogenic, low protein-binding filter (pore size 0.22 micrometer or less).
6. Do not infuse SIMPONI ARIA concomitantly in the same intravenous line with other agents. No physical biochemical compatibility studies have been conducted to evaluate the use of SIMPONI ARIA with other intravenous agents in the same intravenous line.
7. Infuse the diluted solution over 30 minutes.
8. Once diluted, the infusion solution can be stored for up to 4 hours at room temperature.

3 DOSAGE FORMS AND STRENGTHS

Injection: 50 mg/4 mL (12.5 mg/mL) colorless to light yellow solution in a single-dose vial.

4 CONTRAINDICATIONS

None.

5 WARNINGS AND PRECAUTIONS

5.1 Serious Infections

Patients treated with SIMPONI ARIA are at increased risk for developing serious infections involving various organ systems and sites that may lead to hospitalization or death.

Opportunistic infections due to bacterial, mycobacterial, invasive fungal, viral, or parasitic organisms including aspergillosis, blastomycosis, candidiasis, coccidioidomycosis, histoplasmosis, legionellosis, listeriosis, pneumocystosis, and tuberculosis have been reported with TNF-blockers. Patients have frequently presented with disseminated rather than localized disease. The concomitant use of a TNF-blocker and abatacept or anakinra was associated with a higher risk of serious infections; therefore, the concomitant use of SIMPONI ARIA and these biologic products is not recommended [see Warnings and Precautions (5.6, 5.7)and Drug Interactions (7.2)] .

Treatment with SIMPONI ARIA should not be initiated in patients with an active infection, including clinically important localized infections. Patients greater than 65 years of age, patients with co-morbid conditions and/or patients taking concomitant immunosuppressants such as corticosteroids or methotrexate may be at greater risk of infection. Consider the risks and benefits of treatment prior to initiating SIMPONI ARIA in patients:

- with chronic or recurrent infection;
- who have been exposed to tuberculosis;
- with a history of an opportunistic infection;
- who have resided or traveled in areas of endemic tuberculosis or endemic mycoses, such as histoplasmosis, coccidioidomycosis, or blastomycosis; or
- with underlying conditions that may predispose them to infection.

Monitoring

Closely monitor patients for the development of signs and symptoms of infection during and after treatment with SIMPONI ARIA. Discontinue SIMPONI ARIA if a patient develops a serious infection, an opportunistic infection, or sepsis. For patients who develop a new infection during treatment with SIMPONI ARIA, perform a prompt and complete diagnostic workup appropriate for an immunocompromised patient and initiate appropriate antimicrobial therapy and closely monitor them.

Tuberculosis

Cases of reactivation of tuberculosis or new tuberculosis infections have been observed in patients receiving TNF-blockers, including patients who have previously received treatment for latent or active tuberculosis. Evaluate patients for tuberculosis risk factors and test for latent infection prior to initiating SIMPONI ARIA and periodically during therapy.

Treatment of latent tuberculosis infection prior to therapy with TNF-blockers has been shown to reduce the risk of tuberculosis reactivation during therapy. Prior to initiating SIMPONI ARIA, assess if treatment for latent tuberculosis is needed; An induration of 5 mm or greater is a positive tuberculin skin test, even for patients previously vaccinated with Bacille Calmette-Guerin (BCG).

Consider anti-tuberculosis therapy prior to initiation of SIMPONI ARIA in patients with a past history of latent or active tuberculosis in whom an adequate course of treatment cannot be confirmed, and for patients with a negative test for latent tuberculosis but having risk factors for tuberculosis infection. Consultation with a physician with expertise in the treatment of tuberculosis is recommended to aid in the decision whether initiating anti-tuberculosis therapy is appropriate for an individual patient.

Cases of active tuberculosis have occurred in patients treated with the subcutaneous formulation of golimumab during and after treatment for latent tuberculosis. Monitor patients for the development of signs and symptoms of tuberculosis including patients who tested negative for latent tuberculosis infection prior to initiating therapy, patients who are on treatment for latent tuberculosis, or patients who were previously treated for tuberculosis infection.

Consider tuberculosis in the differential diagnosis in patients who develop a new infection during SIMPONI ARIA treatment, especially in patients who have previously or recently traveled to countries with a high prevalence of tuberculosis, or who have had close contact with a person with active tuberculosis.

Invasive Fungal Infections

If patients develop a serious systemic illness and they reside or travel in regions where mycoses are endemic, consider invasive fungal infection in the differential diagnosis. Consider appropriate empiric antifungal therapy and take into account both the risk for severe fungal infection and the risks of antifungal therapy while a diagnostic workup is being performed. Antigen and antibody testing for histoplasmosis may be negative in some patients with active infection. To aid in the management of such patients, consider consultation with a physician with expertise in the diagnosis and treatment of invasive fungal infections.

Hepatitis B Virus Reactivation

The use of TNF-blockers, of which SIMPONI ARIA is a member, has been associated with reactivation of hepatitis B virus (HBV) in patients who are chronic hepatitis B carriers (i.e., surface antigen positive). In some instances, HBV reactivation occurring in conjunction with TNF-blocker therapy has been fatal. The majority of these reports have occurred in patients who received concomitant immunosuppressants.

All patients should be tested for HBV infection before initiating TNF-blocker therapy. For patients who test positive for hepatitis B surface antigen, consultation with a physician with expertise in the treatment of hepatitis B is recommended before initiating TNF-blocker therapy. The risks and benefits of treatment should be considered prior to prescribing TNF-blockers, including SIMPONI ARIA, to patients who are carriers of HBV. Adequate data are not available on whether antiviral therapy can reduce the risk of HBV reactivation in HBV carriers who are treated with TNF-blockers. Patients who are carriers of HBV and require treatment with TNF-blockers should be closely monitored for clinical and laboratory signs of active HBV infection throughout therapy and for several months following termination of therapy.

In patients who develop HBV reactivation, TNF-blockers should be stopped and antiviral therapy with appropriate supportive treatment should be initiated. The safety of resuming TNF-blockers after HBV reactivation has been controlled is not known. Therefore, prescribers should exercise caution when considering resumption of TNF-blockers in this situation and monitor patients closely.

5.2 Malignancies

Malignancies in Pediatric Patients

Malignancies, some fatal, have been reported among children, adolescents, and young adults who received treatment with TNF-blocking agents (initiation of therapy ≤ 18 years of age), including golimumab. Approximately half the cases were lymphomas, including Hodgkin's and non-Hodgkin's lymphoma. The other cases represented a variety of malignancies, including rare malignancies that are usually associated with immunosuppression, and malignancies that are not usually observed in children and adolescents. The malignancies occurred after a median of 30 months (range 1 to 84 months) after the first dose of TNF-blocker therapy. Most of the patients were receiving concomitant immunosuppressants. Most cases were reported postmarketing and are derived from a variety of sources, including registries and spontaneous postmarketing reports.

Malignancies in Adult Patients

The risks and benefits of TNF-blocker treatment including SIMPONI ARIA should be considered prior to initiating therapy in patients with a known malignancy other than a successfully treated non-melanoma skin cancer (NMSC) or when considering continuing a TNF-blocker in patients who develop a malignancy.

In the controlled portions of clinical trials of TNF-blockers including the subcutaneous formulation of golimumab more cases of lymphoma have been observed among patients receiving anti-TNF treatment compared with patients in the control groups. Patients with RA and other chronic inflammatory diseases, particularly patients with highly active disease and/or chronic exposure to immunosuppressant therapies, may be at higher risk (up to several fold) than the general population for the development of lymphoma, even in the absence of TNF-blocking therapy. Cases of acute and chronic leukemia have been reported with TNF-blocker use, including SIMPONI ARIA, in rheumatoid arthritis and other indications. Even in the absence of TNF-blocker therapy, patients with rheumatoid arthritis may be at a higher risk (approximately 2-fold) than the general population for the development of leukemia.

Rare postmarketing cases of hepatosplenic T-cell lymphoma (HSTCL) have been reported in patients treated with TNF-blocking agents. This rare type of T-cell lymphoma has a very aggressive disease course and is usually fatal. Nearly all of the reported TNF-blocker associated cases have occurred in patients with Crohn's disease or ulcerative colitis. The majority were in adolescent and young adult males. Almost all these patients had received treatment with azathioprine (AZA) or 6-mercaptopurine (6–MP) concomitantly with a TNF-blocker at or prior to diagnosis. A risk for the development for hepatosplenic T-cell lymphoma in patients treated with TNF-blockers cannot be excluded.

Melanoma and Merkel cell carcinoma have been reported in patients treated with TNF-blocking agents, including SIMPONI ARIA. Periodic skin examination is recommended for all patients, particularly those with risk factors for skin cancer.

In controlled trials of other TNF-blockers in patients at higher risk for malignancies (e.g., patients with chronic obstructive pulmonary disease [COPD], patients with Wegener's granulomatosis treated with concomitant cyclophosphamide) a greater portion of malignancies occurred in the TNF-blocker group compared to the controlled group. In an exploratory clinical trial evaluating the use of the subcutaneous formulation of golimumab in patients with severe persistent asthma, more patients treated with golimumab reported malignancies compared with control patients. The significance of this finding is unknown.

During the controlled portion of the Phase 3 trial in RA for SIMPONI ARIA, the incidence of malignancies other than lymphoma and NMSC per 100-patient-years of follow-up was 0.56 (95% CI: 0.01, 3.11) in the SIMPONI ARIA group compared with an incidence of 0 (95% CI: 0.00, 3.79) in the placebo group.

5.3 Congestive Heart Failure

Cases of worsening congestive heart failure (CHF) and new onset CHF have been reported with TNF-blockers, including SIMPONI ARIA. Some cases had a fatal outcome. In several exploratory trials of other TNF-blockers in the treatment of CHF, there were greater proportions of TNF-blocker treated patients who had CHF exacerbations requiring hospitalization or increased mortality. SIMPONI ARIA has not been studied in patients with a history of CHF and SIMPONI ARIA should be used with caution in patients with CHF. If a decision is made to administer SIMPONI ARIA to patients with CHF, these patients should be closely monitored during therapy, and SIMPONI ARIA should be discontinued if new or worsening symptoms of CHF appear.

5.4 Demyelinating Disorders

Use of TNF-blockers, including SIMPONI ARIA, has been associated with rare cases of new onset or exacerbation of central nervous system (CNS) demyelinating disorders, including multiple sclerosis (MS), and peripheral demyelinating disorders, including Guillain-Barré syndrome. Cases of central demyelination, MS, optic neuritis, and peripheral demyelinating polyneuropathy have rarely been reported in patients treated with golimumab. Prescribers should exercise caution in considering the use of TNF-blockers, including SIMPONI ARIA, in patients with central or peripheral nervous system demyelinating disorders. Discontinuation of SIMPONI ARIA should be considered if these disorders develop.

5.5 Autoimmunity

Treatment with TNF blockers, including SIMPONI ARIA, may result in the formation of antinuclear antibodies (ANA). Rarely, treatment with TNF blockers, may result in the development of a lupus-like syndrome [see Adverse Reactions (6.1)] . If a patient develops symptoms suggestive of a lupus-like syndrome following treatment with SIMPONI ARIA, treatment should be discontinued.

5.6 Use with Abatacept

In controlled trials, the concurrent administration of another TNF-blocker and abatacept was associated with a greater proportion of serious infections than the use of a TNF-blocker alone; and the combination therapy, compared to the use of a TNF-blocker alone, has not demonstrated improved clinical benefit in the treatment of RA. Therefore, the combination of TNF-blockers, including SIMPONI ARIA, and abatacept is not recommended [see Drug Interactions (7.2)] .

5.7 Use with Anakinra

Concurrent administration of anakinra (an interleukin-1 antagonist) and another TNF-blocker was associated with a greater portion of serious infections and neutropenia and no additional benefits compared with the TNF-blocker alone. Therefore, the combination of anakinra with TNF-blockers, including SIMPONI ARIA, is not recommended [see Drug Interactions (7.2)] .

5.8 Switching Between Biological Disease Modifying Antirheumatic Drugs (DMARDs)

Care should be taken when switching from one biologic product to another biologic product since overlapping biological activity may further increase the risk of infection.

5.9 Hematologic Cytopenias

There have been reports of pancytopenia, leukopenia, neutropenia, agranulocytosis, aplastic anemia, and thrombocytopenia in patients receiving golimumab. Caution should be exercised when using TNF-blockers, including SIMPONI ARIA, in patients who have or have had significant cytopenias.

5.10 Vaccinations/Therapeutic Infectious Agents

Live Vaccines

Avoid live vaccines in patients treated with SIMPONI ARIA. In patients receiving anti-TNF therapy, limited data are available on the response to live vaccination, or on the secondary transmission of infection by live vaccines. Use of live vaccines could result in clinical infections, including disseminated infections.

Administration of live vaccines to infants exposed to SIMPONI ARIA in uterois not recommended for 6 months following the mother's last SIMPONI ARIA infusion during pregnancy [see Drug Interactions (7.3)and Use in Specific Populations (8.1)] .

Whenever possible update immunizations prior to initiation of treatment with SIMPONI ARIA following current immunization guidelines for patients receiving immunosuppressive agents. Advise patients to discuss with the physician before seeking any immunizations.

Therapeutic Infectious Agents

Other uses of therapeutic infectious agents such as live attenuated bacteria (e.g., BCG bladder instillation for the treatment of cancer) could result in clinical infections, including disseminated infections. It is recommended that therapeutic infectious agents not be given concurrently with SIMPONI ARIA.

5.11 Hypersensitivity Reactions

In postmarketing experience, serious systemic hypersensitivity reactions (including anaphylaxis) have been reported following administration of the subcutaneous and intravenous formulations of golimumab including SIMPONI ARIA. Hypersensitivity reactions including hives, pruritus, dyspnea, and nausea, were reported during infusion and generally within an hour after infusion. Some of these reactions occurred after the first administration of golimumab. If an anaphylactic or other serious allergic reaction occurs, administration of SIMPONI ARIA should be discontinued immediately and appropriate therapy instituted.

6 ADVERSE REACTIONS

The most serious adverse reactions were:

- Serious Infections [see Warnings and Precautions (5.1)]
- Malignancies [see Warnings and Precautions (5.2)]

6.1 Clinical Trials Experience

Because clinical trials are conducted under widely varying conditions, adverse reaction rates observed in the clinical trials of a drug cannot be directly compared to rates in the clinical trials of another drug and may not reflect the rates observed in clinical practice.

The safety data described below are based on one, randomized, double-blind, controlled Phase 3 trial in patients with RA receiving SIMPONI ARIA by intravenous infusion (Trial RA). The protocol included provisions for patients taking placebo to receive treatment with SIMPONI ARIA at Week 16 or Week 24 either by patient response (based on uncontrolled disease activity) or by design, so that adverse events cannot always be unambiguously attributed to a given treatment. Comparisons between placebo and SIMPONI ARIA were based on the first 24 weeks of exposure.

Trial RA included 197 control-treated patients and 463 SIMPONI ARIA-treated patients (which includes control-treated patients who switched to SIMPONI ARIA at Week 16). The proportion of patients who discontinued treatment due to adverse reactions in the controlled phase of Trial RA through Week 24 was 3.5% for SIMPONI ARIA-treated patients and 0.5% for placebo-treated patients. Upper respiratory tract infection was the most common adverse reaction reported in the trial through Week 24 occurring in 6.5% of SIMPONI ARIA-treated patients as compared with 7.6% of control-treated patients, respectively.

Infections

Serious infections observed in SIMPONI ARIA-treated patients included sepsis, pneumonia, cellulitis, abscess, opportunistic infections, tuberculosis (TB), and invasive fungal infections. Cases of TB included pulmonary and extrapulmonary TB. The majority of the TB cases occurred in countries with a high incidence rate of TB [see Warnings and Precautions (5.1)] .

In the controlled phase of Trial RA through Week 24, infections were observed in 27% of SIMPONI ARIA-treated patients compared with 24% of control-treated patients, and serious infections were observed in 0.9% of SIMPONI ARIA-treated patients and 0.0% of control-treated patients. Through Week 24, the incidence of serious infections per 100 patient-years of follow-up was 2.2 (95% CI 0.61, 5.71) for the SIMPONI ARIA group, and 0 (0.00, 3.79) for the placebo group. In the controlled and uncontrolled portions of Trial RA, 958 total patient-years of follow-up with a median follow-up of approximately 92 weeks, the incidence per 100 patient-years of all serious infections was 4.07 (95% CI: 2.90, 5.57) in patients receiving SIMPONI ARIA [see Warnings and Precautions (5.1)] . In the controlled and uncontrolled portions of Trial RA, in SIMPONI ARIA-treated patients, the incidence of active TB per 100 patient-years was 0.31 (95% CI: 0.06; 0.92) and the incidence of other opportunistic infections per 100 patient-years was 0.42 (95% CI: 0.11, 1.07).

Malignancies

One case of malignancy other than lymphoma and NMSC with SIMPONI ARIA was reported through Week 24 during the controlled phase of Trial RA. In the controlled and uncontrolled portions through approximately 92 weeks, the incidence of malignancies per 100 patient-years, other than lymphoma and NMSC, in SIMPONI ARIA-treated patients was 0.31 (95% CI: 0.06, 0.92) and the incidence of NMSC was 0.1 (95% CI: 0.00, 0.58).

Liver Enzyme Elevations

There have been reports of severe hepatic reactions including acute liver failure in patients receiving TNF-blockers.

In the controlled phase of Trial RA, through Week 24, ALT elevations ≥ 5 × ULN occurred in 0.8% of SIMPONI ARIA-treated patients and 0% of control-treated patients and ALT elevations ≥ 3 × ULN occurred in 2.3% of SIMPONI ARIA-treated patients and 2.5% of control-treated patients.

In the controlled phase of Trial PsA, through Week 24, ALT elevations ≥ 5 × ULN occurred in 1.7% of SIMPONI ARIA-treated patients and <1% of placebo-treated patients, and ALT elevations ≥ 3 × ULN to < 5 × ULN occurred in 2.9% of SIMPONI ARIA-treated patients and <1% of placebo-treated patients.

Since many of the patients in the Phase 3 trials were also taking medications that cause liver enzyme elevations (e.g., nonsteroidal anti-inflammatory drugs [NSAIDs], MTX, or isoniazid prophylaxis), the relationship between SIMPONI ARIA and liver enzyme elevation is not clear.

Autoimmune Disorders and Autoantibodies

At Week 20 in Trial RA, 17% of SIMPONI ARIA-treated patients and 13% of control patients were newly antinuclear antibody (ANA)-positive. Of these patients, one SIMPONI ARIA-treated patient and no control-treated patients had newly positive anti-dsDNA antibodies [see Warnings and Precautions (5.5)] .

Administration Reactions

In the controlled phase of Trial RA through Week 24, 1.1% of SIMPONI ARIA infusions were associated with an infusion reaction compared with 0.2% of infusions in the control group. The most common infusion reaction in SIMPONI ARIA-treated patients was rash. No serious infusion reactions were reported.

Other Adverse Reactions

Table 1 summarizes the adverse drug reactions that occurred at a rate of at least 1% in the SIMPONI ARIA + MTX group with a higher incidence than in the placebo + MTX group during the controlled period of Trial RA through Week 24.

Table 1: Adverse Drug Reactions Reported by ≥ 1% of SIMPONI ARIA-Treated Patients and with a Higher Incidence than Placebo-Treated Patients in Trial RA through Week 24
 | Placebo + MTX | SIMPONI ARIA + MTX
Patients treated | 197 | 463
Adverse Reaction
Infections and infestations
Upper respiratory tract infection (such as upper respiratory tract infection, nasopharyngitis, pharyngitis, laryngitis, and rhinitis) | 12% | 13%
Viral infections (such as influenza and herpes) | 3% | 4%
Bacterial infections | 0% | 1%
Bronchitis | 1% | 3%
Vascular disorders
Hypertension | 2% | 3%
Skin and subcutaneous disorders
Rash | 1% | 3%
General disorders and administration site conditions
Pyrexia | 1% | 2%
Blood and lymphatic disorders
Leukopenia | 0% | 1%

Other and Less Common Clinical Trial Adverse Drug Reactions

Adverse drug reactions that do not appear in Table 1 or that occurred < 1% in SIMPONI ARIA-treated patients during Trial RA through Week 24 that do not appear in the Warnings and Precautions section included the following events listed by system organ class:

Infections and infestations:Superficial fungal infection, sinusitis, abscess, lower respiratory tract infection (pneumonia), pyelonephritis

Investigations:Alanine aminotransferase (ALT) increased, aspartate aminotransferase (AST) increased, neutrophil count decreased

Nervous system disorders:Dizziness, paresthesia

Gastrointestinal disorders:Constipation

Psoriatic Arthritis

Trial PsA evaluated 480 patients [see Clinical Studies (14.2)] . The adverse reactions were similar to those observed in patients with RA, with the exception of psoriasis (new onset or worsening, palmar/plantar and pustular), which occurred in <1% of SIMPONI ARIA-treated patients. The incidence of the adverse reactions reported in Trial PsA were similar to Trial RA with the exceptions of higher incidence in SIMPONI ARIA for ALT increased (7.9% vs. 2.1% in placebo), AST increased (5.4% vs. 2.1% in placebo), and neutrophil count decreased (4.6% vs. 2.1% in placebo).

Ankylosing Spondylitis

Trial AS evaluated 208 patients [see Clinical Studies (14.3)] . The adverse reactions were similar to those reported in patients with RA, with the exception of the higher incidence of ALT increased, which occurred in 2.9% of SIMPONI ARIA-treated patients compared with none of the placebo-treated patients.

Pediatric Patients with Polyarticular Juvenile Idiopathic Arthritis and Psoriatic Arthritis

Trial pJIA evaluated 127 patients with JIA with active polyarthritis [see Use in Specific Populations (8.4)and Clinical Studies (14.4)]. The adverse reactions observed were consistent with the established safety profile of SIMPONI ARIA in adult patients with RA and PsA.

6.2 Immunogenicity

As with all therapeutic proteins, there is potential for immunogenicity. The detection of antibody formation is highly dependent on the sensitivity and specificity of the assay. Additionally, the observed incidence of antibody (including neutralizing antibody) positivity in an assay may be influenced by several factors including assay methodology, sample handling, timing of sample collection, concomitant medications, and underlying disease. For these reasons, comparison of the incidence of antibodies to golimumab in the trials described below with the incidence of antibodies in other trials or to other products may be misleading.

Using an enzyme immunoassay (EIA) method, antibodies to golimumab were detected in 13 (3%) golimumab-treated patients following IV administration of SIMPONI ARIA in combination with MTX through Week 24 of Trial RA, of which all were neutralizing antibodies.

A drug-tolerant enzyme immunoassay (drug-tolerant EIA) method for detecting antibodies to golimumab was developed and validated. This method is approximately 16-fold more sensitive than the original EIA method with less interference from golimumab in serum. Through approximately 6 months, the incidence of antibodies to golimumab with the drug-tolerant EIA method for Trials RA, PsA, AS, and pJIA was 21%, 19%, 19% and 31%, respectively. Where tested, approximately one-third to one-half were neutralizing.

Patients with RA, PsA, AS and pJIA who developed antibodies to golimumab generally had lower trough steady-state serum concentrations of golimumab [see Clinical Pharmacology (12.3)].

6.3 Postmarketing Experience

The following adverse reactions have been identified during post-approval use of golimumab. Because these reactions are reported voluntarily from a population of uncertain size, it is not always possible to reliably estimate their frequency or establish a causal relationship to golimumab exposure:

General Disorders and Administration Site Conditions:Infusion-related reactions [see Warnings and Precautions (5.11)]

Neoplasm benign and malignant: Melanoma, Merkel cell carcinoma [see Warnings and Precautions (5.2)]

Immune system disorders: Serious systemic hypersensitivity reactions (including anaphylactic reaction) [see Warnings and Precautions (5.11)] , sarcoidosis

Respiratory, thoracic and mediastinal disorders: Interstitial lung disease

Skin and subcutaneous tissue disorders: Skin exfoliation, lichenoid reactions, bullous skin reactions

7 DRUG INTERACTIONS

7.1 Methotrexate

SIMPONI ARIA should be used with MTX for the treatment of RA [see Clinical Studies (14.1)] . Following IV administration, concomitant administration of methotrexate decreases the clearance of SIMPONI ARIA by approximately 9% based on population pharmacokinetics (PK) analysis. In addition, concomitant administration of methotrexate decreases the SIMPONI ARIA clearance by reducing the development of antibodies to golimumab.

7.2 Biologic Products for RA, PsA, AS, and pJIA

An increased risk of serious infections has been seen in clinical RA studies of other TNF-blockers used in combination with anakinra or abatacept, with no added benefit; therefore, use of SIMPONI ARIA with other biologic products, including abatacept or anakinra, is not recommended [see Warnings and Precautions (5.6and 5.7)] . A higher rate of serious infections has also been observed in RA patients treated with rituximab who received subsequent treatment with a TNF-blocker. The concomitant use of SIMPONI ARIA with biologics approved to treat RA, PsA, AS, and pJIA is not recommended because of the possibility of an increased risk of infection.

7.3 Live Vaccines/Therapeutic Infectious Agents

Live vaccines should not be given concurrently with SIMPONI ARIA [see Warnings and Precautions (5.10)] .

Therapeutic infectious agents should not be given concurrently with SIMPONI ARIA [see Warnings and Precautions (5.10)] .

Infants born to women treated with SIMPONI ARIA during their pregnancy may be at increased risk of infection for up to 6 months. Administration of live vaccines to infants exposed to SIMPONI ARIA in uterois not recommended for 6 months following the mother's last SIMPONI ARIA infusion during pregnancy [see Warnings and Precautions (5.10), Use in Specific Populations (8.1)] .

7.4 Cytochrome P450 Substrates

The formation of CYP450 enzymes may be suppressed by increased levels of cytokines (e.g., TNFα) during chronic inflammation. Therefore, it is expected that for a molecule that antagonizes cytokine activity, such as golimumab, the formation of CYP450 enzymes could be normalized. Upon initiation or discontinuation of SIMPONI ARIA in patients being treated with CYP450 substrates with a narrow therapeutic index, monitoring of the effect (e.g., warfarin) or drug concentration (e.g., cyclosporine or theophylline) is recommended and the individual dose of the drug product may be adjusted as needed.

8 USE IN SPECIFIC POPULATIONS

8.1 Pregnancy

Risk Summary

Available data from postmarketing case reports with golimumab use in pregnant women have not identified a drug-associated risk of major birth defects, miscarriage, or adverse maternal or fetal outcomes. An observational study of northern European births observed similar unadjusted rates of major birth defects in infants exposed in utero to golimumab compared to no treatment or non-biologic systemic therapy. However, this study had important limitations (see Data).

Monoclonal antibodies, such as golimumab, are transported across the placenta during the third trimester of pregnancy and may affect immune response in the in uteroexposed infant. There are clinical considerations for the use of SIMPONI ARIA in pregnant women (see Clinical Considerations) . In an animal reproductive study, golimumab administered by the subcutaneous route to pregnant monkeys, during the period of organogenesis, at doses that produced exposures approximately 200 times the maximum recommended human dose (MRHD) had no adverse fetal effects.

All pregnancies have a background risk of birth defect, loss, or other adverse outcomes. The estimated background risk of major birth defects and miscarriage for the indicated populations is unknown. In the U.S. general population, the estimated background risks of major birth defects and miscarriage in clinically recognized pregnancies is 2–4% and of miscarriage is 15–20%, respectively.

Clinical Considerations

Fetal/Neonatal Adverse Reactions

Golimumab crosses the placenta during pregnancy. Another TNF-blocking monoclonal antibody administered during pregnancy was detected for up to 6 months in the serum of infants. Consequently, these infants may be at increased risk of infection. Administration of live vaccines to infants exposed to SIMPONI ARIA in uterois not recommended for 6 months following the mother's last SIMPONI ARIA infusion during pregnancy [see Warnings and Precautions (5.10)and Drug Interactions (7.3)] .

Data

Human Data

An observational, exposure-based, cohort study based on data from the Swedish, Danish, and Finnish Medical Birth Registers conducted between 2006–2020 (Sweden and Denmark) and 2006–2019 (Finland) compared the risk of major birth defects in 134 live-born infants exposed to golimumab (116 from women treated for rheumatic conditions, 18 from women treated for ulcerative colitis) to no treatment or nonbiologic systemic therapy. The unadjusted rate of major birth defects in infants exposed in uterowas similar across all groups. However, this study had important limitations such as a small number of pregnant women exposed to golimumab, a wide exposure ascertainment window, and incomplete risk adjustment for potential confounders.

Animal Data

In an embryofetal developmental toxicology study in which pregnant cynomolgus monkeys were treated with golimumab during the period of organogenesis from gestation days (GD) 20 to 51, exposures up to 200 times greater than the exposure at the MRHD (on an area under the curve (AUC) basis with maternal subcutaneous doses up to 50 mg/kg twice weekly) produced no evidence of fetal malformations or embryotoxicity. There was no evidence of maternal toxicity. Umbilical cord blood samples collected at the end of the second trimester showed that fetuses were exposed to golimumab during gestation.

In a pre- and postnatal developmental study in which pregnant cynomolgus monkeys were treated with golimumab from gestation day 50 to postpartum day 33, maximal drug concentrations up to 33 times greater than that found with the MRHD (on a maximum blood concentration (Cmax) basis at steady-state with maternal subcutaneous doses up to 50 mg/kg twice weekly) were not associated with any evidence of developmental defects in infants. There was no evidence of maternal toxicity. Golimumab was present in fetal serum at the end of the second trimester and in neonatal serum from the time of birth and for up to 6 months postpartum.

8.2 Lactation

Risk Summary

There is no information regarding the presence of SIMPONI ARIA in human milk, the effects on breastfed infants, or the effects on milk production. Maternal IgG is known to be present in human milk. Golimumab is present in the milk of lactating cynomolgus monkeys (see Data) . If golimumab is transferred into human milk, the effects of local exposure in the gastrointestinal tract and potential limited systemic exposure in the infant to golimumab are unknown. The developmental and health benefits of breast-feeding should be considered along with the mother's clinical need for SIMPONI ARIA and any potential adverse effects on the breast-fed infants from SIMPONI ARIA, or from the underlying maternal condition.

Data

In the pre- and postnatal development study in cynomolgus monkeys in which golimumab was administered subcutaneously during pregnancy and lactation, golimumab was detected in the breast milk at concentrations that were approximately 400 fold lower than the maternal serum concentrations.

8.4 Pediatric Use

Safety and effectiveness of SIMPONI ARIA for active polyarticular juvenile idiopathic arthritis and PsA have been established in pediatric patients 2 years and older.

Use of SIMPONI ARIA in these age groups is supported by evidence from adequate and well-controlled studies of SIMPONI ARIA in adults with RA and PsA, pharmacokinetic data from adult patients with RA and PsA and pediatric patients with JIA with active polyarthritis, and safety data from a clinical study in 127 pediatric patients 2 to < 18 years of age with JIA with active polyarthritis. The observed pre-dose (trough) concentrations are generally comparable between adults with RA and PsA and pediatric patients with JIA with active polyarthritis, and the PK exposure is expected to be comparable between adult PsA and pediatric patients with PsA [see Adverse Reactions (6.1), Clinical Pharmacology (12.3)and Clinical Studies (14.2, 14.4)] .

Malignancies, some fatal, have been reported among children, adolescents, and young adults who received treatment with golimumab and other TNF-blocking agents [see Warnings and Precautions (5.2)].

The safety and effectiveness in pediatric patients below the age of 2 years have not been established in pJIA or in PsA. The safety and effectiveness of SIMPONI ARIA in pediatric patients with conditions other than pJIA and PsA have not been established.

8.5 Geriatric Use

In Trial RA, the number of patients ages 65 or older was too small to make comparisons with younger SIMPONI ARIA-treated patients. Because there is a higher incidence of infections in the geriatric population in general, caution should be used in treating geriatric patients with SIMPONI ARIA.

10 OVERDOSAGE

In a clinical study, 5 patients received single infusions of up to 1000 mg of SIMPONI ARIA without serious adverse reactions or other significant reactions.

11 DESCRIPTION

Golimumab is a human IgG1қ monoclonal antibody specific for human tumor necrosis factor alpha (TNFα) that exhibits multiple glycoforms with molecular masses of approximately 150 to 151 kilodaltons. Golimumab was created using genetically engineered mice immunized with human TNF, resulting in an antibody with human-derived antibody variable and constant regions. Golimumab is produced by a recombinant cell line cultured by continuous perfusion and is purified by a series of steps that includes measures to inactivate and remove viruses.

The SIMPONI ARIA®(golimumab) Injection is a sterile solution of the golimumab antibody supplied in a 4-mL glass vial for intravenous infusion.

SIMPONI ARIA is a preservative-free, colorless to light yellow solution with a pH of approximately 5.5. SIMPONI ARIA is not made with natural rubber latex. Each 4-mL vial of SIMPONI ARIA contains 50 mg golimumab, L-histidine (1.14 mg), L-histidine monohydrochloride monohydrate (6.42 mg), polysorbate 80 (0.6 mg), sorbitol (180 mg), and water for injection.

12 CLINICAL PHARMACOLOGY

12.1 Mechanism of Action

Golimumab is a human monoclonal antibody that binds to both the soluble and transmembrane bioactive forms of human TNFα. This interaction prevents the binding of TNFα to its receptors, thereby inhibiting the biological activity of TNFα (a cytokine protein). There was no evidence of the golimumab antibody binding to other TNF superfamily ligands; in particular, the golimumab antibody did not bind or neutralize human lymphotoxin. Golimumab did not lyse human monocytes expressing transmembrane TNF in the presence of complement or effector cells.

Elevated TNFα levels in the blood, synovium, and joints have been implicated in the pathophysiology of several chronic inflammatory diseases such as rheumatoid arthritis, psoriatic arthritis and ankylosing spondylitis. TNFα is an important mediator of the articular inflammation that is characteristic of these diseases. Golimumab modulated the in vitrobiological effects mediated by TNF in several bioassays, including the expression of adhesion proteins responsible for leukocyte infiltration (E-selectin, ICAM-1 and VCAM-1) and the secretion of proinflammatory cytokines (IL-6, IL-8, G-CSF and GM-CSF). The clinical relevance of these findings is unknown.

12.2 Pharmacodynamics

Following treatment with SIMPONI ARIA in patients with RA, decreases from baseline were observed in tissue inhibitor of metalloproteinase-1 (TIMP-1), matrix metalloproteinase-1 (MMP-1), matrix metalloproteinase-3 (MMP-3), resistin, interleukin-6 (IL-6), macrophage inflammatory protein-1 (MIP-1b), vascular endothelial growth factor (VEGF), serum amyloid A (SAA), S100A12, and high sensitivity C-Reactive protein (hsCRP). Conversely, increases from baseline were observed in tartrate-resistant acid phosphatase (TRAP-5b). The clinical relevance of this information is not known.

12.3 Pharmacokinetics

Golimumab exhibited approximately dose-proportional pharmacokinetics in patients with RA over the dose range of 0.1 to 10.0 mg/kg following a single intravenous dose.

Absorption

Following a single intravenous administration of 2 mg/kg SIMPONI ARIA, a mean Cmaxof 44.4 ± 11.3 mcg/mL was observed in patients with RA. Data directly comparing 2 mg/kg intravenous administration and 50 mg subcutaneous administration are not available.

Distribution

Following a single intravenous administration of 2 mg/kg SIMPONI ARIA, the mean volume of distribution was estimated to be 115 ± 19 mL/kg in healthy subjects, and 151 ± 61 mL/kg in patients with RA. The volume of distribution of golimumab may indicate that golimumab is distributed primarily in the circulatory system with limited extravascular distribution.

Elimination

Following a single intravenous administration of 2 mg/kg SIMPONI ARIA, the systemic clearance of golimumab was estimated to be 6.9 ± 2.0 mL/day/kg in healthy subjects and 7.6 ± 2.0 mL/day/kg in patients with RA. The mean terminal half-life was estimated to be 12 ± 3 days in healthy subjects and the mean terminal half-life in RA patients was 14 ± 4 days.

Multiple Doses

When 2 mg/kg SIMPONI ARIA was administered intravenously to patients with RA at weeks 0, 4 and every 8 weeks thereafter, serum concentrations reached steady-state by Week 12. With concomitant use of MTX, treatment with 2 mg/kg SIMPONI ARIA every 8 weeks resulted in a mean steady-state trough serum concentration of approximately 0.4 ± 0.4 mcg/mL in patients with active RA. The mean steady-state trough serum concentration in patients with PsA was 0.7 ± 0.6 mcg/mL. The mean steady-state trough serum concentration in patients with AS was 0.8 ± 0.6 mcg/mL.

Patients with RA, PsA and AS who developed antibodies to golimumab generally had lower trough steady-state serum concentrations of golimumab [see Adverse Reactions (6.2)].

Specific Populations

No formal study of the effect of renal or hepatic impairment on the PK of golimumab was conducted.

Body Weight

Following intravenous administration, patients with higher body weight tended to have slightly higher serum golimumab concentrations than patients with lower body weights when golimumab was administered on a mg/kg (body weight) basis. However, based on population PK analysis, there were no clinically relevant differences in golimumab exposure following intravenous administration of 2 mg/kg SIMPONI ARIA in adult patients across a range of different body weights.

Pediatrics

When 80 mg/m^2SIMPONI ARIA was administered intravenously to patients with JIA with active polyarthritis at weeks 0, 4 and every 8 weeks thereafter, serum concentrations reached steady-state by Week 12. With concomitant use of MTX, treatment with 80 mg/m^2SIMPONI ARIA resulted in a mean steady-state trough serum golimumab concentration of approximately 0.5 ± 0.4 mcg/mL and a mean steady-state AUC of 425 ± 125 mcg∙day/mL in patients with JIA with active polyarthritis. Overall, the observed steady-state golimumab trough concentrations in patients with JIA with active polyarthritis were within the range of those observed for adult RA and PsA after administration of SIMPONI ARIA.

Consistent with the intravenous data in adult patients with RA, population pharmacokinetic analyses for intravenous SIMPONI ARIA in pJIA revealed that there were no clinically relevant differences in golimumab exposure following intravenous administration of 80 mg/m^2SIMPONI ARIA in pediatric patients across a range of age and different body weights. The immune response effect on golimumab clearance in patients with JIA with active polyarthritis was comparable to adults with RA.

Drug Interaction Studies

Specific drug interaction studies have not been conducted with SIMPONI ARIA.

Population PK analysis indicated that concomitant use of MTX, NSAIDs, oral corticosteroids, or sulfasalazine (SSZ) did not significantly influence the clearance of golimumab following IV administration.

13 NONCLINICAL TOXICOLOGY

13.1 Carcinogenesis, Mutagenesis, Impairment of Fertility

Long-term animal studies of golimumab have not been conducted to evaluate its carcinogenic potential. Mutagenicity studies have not been conducted with golimumab. A fertility study conducted in mice using an analogous anti-mouse TNFα antibody administered by the intravenous route at doses up to 40 mg/kg once per week showed no impairment of fertility.

14 CLINICAL STUDIES

14.1 Rheumatoid Arthritis

The efficacy and safety of SIMPONI ARIA were evaluated in one multicenter, randomized, double-blind, controlled trial (Trial RA, NCT00973479) in 592 patients ≥ 18 years of age with moderately to severely active RA despite concurrent MTX therapy and had not previously been treated with a biologic TNF-blocker. Patients were diagnosed according to the American College of Rheumatology (ACR) criteria, at least 3 months prior to administration of study agent and were required to have at least 6 swollen and 6 tender joints. Patients were randomized to receive either SIMPONI ARIA 2 mg/kg (N=395) or placebo (N=197) over a 30-minute intravenous infusion at Weeks 0, 4 and every 8 weeks thereafter in addition to their weekly maintenance MTX dose (15–25 mg). All patients receiving placebo + MTX received SIMPONI ARIA + MTX after Week 24, but the trial remained blinded until all patients had completed 108 weeks of treatment. Efficacy data were collected and analyzed through Week 52. Patients were allowed to continue stable doses of concomitant low dose corticosteroids (equivalent to ≤ 10 mg of prednisone a day) and/or NSAIDs. The use of other DMARDs including cytotoxic agents or other biologics was prohibited.

The primary endpoint in Trial RA was the percentage of patients achieving an ACR 20 response at Week 14. In Trial RA, the majority of subjects were women (82%) and were Caucasian (80%) with a median age of 52 years and a median weight of 70 kg. Median disease duration was 4.7 years, and 50% of the patients used at least one DMARD other than MTX in the past. At baseline, 81% of patients received concomitant NSAIDs and 81% of patients received low-dose corticosteroids (equivalent to ≤ 10 mg of prednisone a day). The median baseline DAS28-CRP was 5.9 and the median van der Heijde-Sharp score at baseline was 28.5.

Clinical Response

A greater percentage of patients treated with the combination of SIMPONI ARIA + MTX achieved ACR 20 at Week 14 and ACR 50 at Week 24 versus patients treated with the placebo + MTX as shown in Table 2. The percent of patients achieving ACR 20 responses by visit for Trial RA is shown in Figure 1.

Table 2: Trial RA – Proportion of Patients with an ACR Response
Trial RA
Active RA, despite MTX
 | Placebo + MTX | SIMPONI ARIA + MTX | 95% CI [For difference in proportions.]
N [N reflects randomized patients.] | 197 | 395
ACR 20
Week 14 | 25% | 59% | 25.9, 41.4
Week 24 | 32% | 63% | 23.3, 39.4
ACR 50
Week 14 | 9% | 30% | 15.3, 27.2
Week 24 | 13% | 35% | 15.1, 28.4
ACR 70
Week 14 | 3% | 12% | 5.3, 13.4
Week 24 | 4% | 18% | 8.8, 18.1

Figure 1: Trial RA – Percent of Patients Achieving ACR 20 Response Over Time: Randomized Patients

The analysis is based on the intent-to-treat population. Last observation carried forward was performed for missing data. Patients who discontinued treatment due to lack of efficacy were counted as non-responders, as were patients who started prohibited medication or failed to achieve at least a 10% improvement in joint counts at Week 16.

The improvement in all components of the ACR response criteria for the SIMPONI ARIA + MTX group was greater compared to the placebo + MTX group in Trial RA as shown in Table 3.

Table 3: Trial RA ─ Components of ACR Response at Week 14
Trial RA
Active RA, despite MTX
 | Placebo + MTX | SIMPONI ARIA + MTX
N [N reflects randomized patients; actual number of patients evaluable for each endpoint may vary.] | 197 | 395
Number of swollen joints (0–66)
Baseline | 15 | 15
Week 14 | 11 | 6
Number of tender joints (0–68)
Baseline | 26 | 26
Week 14 | 20 | 13
Patient's assessment of pain (0–10)
Baseline | 6.5 | 6.5
Week 14 | 5.6 | 3.9
Patient's global assessment of disease activity (0–10)
Baseline | 6.5 | 6.5
Week 14 | 5.5 | 4.0
Physician's global assessment of disease activity (0–10)
Baseline | 6.3 | 6.2
Week 14 | 4.9 | 3.1
HAQ score (0–3)
Baseline | 1.6 | 1.6
Week 14 | 1.4 | 1.1
CRP (mg/dL) (0–1)
Baseline | 2.2 | 2.8
Week 14 | 1.8 | 0.9
Note: All values are means.

At Week 14, a greater proportion of patients treated with SIMPONI ARIA + MTX achieved a low level of disease activity as measured by a DAS28-CRP less than 2.6 compared with the placebo + MTX group (15% compared to 5%; 95% CI for difference [6.3%, 15.5%]).

Radiographic Response

In Trial RA, structural joint damage was assessed radiographically and expressed as a change in van der Heijde-Modified Sharp Score (vdH-S) and its components, the erosion score and Joint Space Narrowing (JSN) score, at Week 24 compared to baseline. The SIMPONI ARIA + MTX treatment group inhibited the progression of structural damage compared with placebo + MTX, as assessed by total vdH-S score as shown in Table 4.

Table 4: Trial RA – Radiographic Change From Baseline at Week 24
 | Placebo + MTX (N=197) [N reflects randomized patients.] | SIMPONI ARIA + MTX (N=395) , [p-value is displayed only for the major secondary endpoint.]
 | Mean | Mean
Change Total vdH-S Score | 1.1 | 0.03 [p≤0.001.]
Change Erosion Score | 0.5 | -0.1
Change JSN Score | 0.6 | 0.1

At Week 24, a greater proportion of patients in the SIMPONI ARIA + MTX group (71%) had no progression of structural damage (change in the total vdH-S score ≤ 0), compared to 57% of patients in the placebo + MTX group. At Week 52, the mean change from baseline in total vdH-S score was 1.2 in patients originally randomized to placebo + MTX who crossed over to SIMPONI ARIA + MTX at Week 16 or Week 24, and 0.1 in patients originally randomized to SIMPONI ARIA + MTX who remained on active treatment.

Physical Function Response in Patients with RA

Physical function was assessed by the disability index of the Health Assessment Questionnaire (HAQ-DI). At Week 14, the SIMPONI ARIA + MTX group showed greater mean improvement in the HAQ-DI compared with placebo + MTX (0.5 compared to 0.2; 95% CI for difference [0.2, 0.4]).

Other Health-Related Outcomes

General health status was assessed by the 36-item Short Form Health Survey (SF-36). In Trial RA, patients receiving SIMPONI ARIA + MTX demonstrated greater improvement from baseline compared with placebo + MTX in physical component summary (PCS), mental component summary (MCS) scores and in all 8 domains of the SF-36.

Fatigue was assessed by the Functional Assessment of Chronic Illness Therapy-Fatigue score (FACIT-F) in Trial RA. Treatment with SIMPONI ARIA resulted in improvement in fatigue as measured by FACIT-F.

14.2 Psoriatic Arthritis

The efficacy and safety of SIMPONI ARIA were evaluated in a multicenter, randomized, double-blind, placebo-controlled trial in 480 patients ≥ 18 years of age with active psoriatic arthritis despite NSAID or DMARD therapy (Trial PsA, NCT02181673). Previous treatment with a biologic was not allowed. Patients in this trial had a diagnosis of PsA for at least six months and had symptoms of active disease [≥5 swollen joints and ≥5 tender joints and a CRP level of ≥ 0.6 mg/dL]. Patients were randomized to either receive SIMPONI ARIA 2 mg/kg (N=241) or placebo (N=239) as a 30-minute intravenous infusion at Weeks 0, 4, 12 and 20. All patients on placebo received SIMPONI ARIA at Week 24, Week 28 and every 8 weeks thereafter through Week 52. Patients in the SIMPONI ARIA treatment group continued to receive SIMPONI ARIA infusions at Week 28 and every 8 weeks through Week 52.

Patients were allowed to continue stable doses of MTX, NSAIDs, and low dose oral corticosteroids (equivalent to ≤ 10 mg of prednisone per day) during the trial. The use of other DMARDs including cytotoxic agents or other biologics was prohibited.

The primary endpoint was the percentage of patients achieving an ACR 20 response at Week 14.

Patients with each subtype of PsA were enrolled, including polyarticular arthritis with absence of rheumatoid nodules (44%), asymmetric peripheral arthritis (19%), distal interphalangeal joint involvement (8.1%), spondylitis with peripheral arthritis (25%), and arthritis mutilans (4.8%). The median duration of PsA disease was 3.5 years, 86% of patients had previously used MTX, and 35% of patients received at least one other DMARD in the past. At baseline, 76% and 54% of the patients had enthesitis and dactylitis, respectively. The median total modified vdH-S score at baseline was 15.5. During the trial, concomitant medications used included MTX (70%), oral corticosteroids (28%), and NSAIDs (71%).

Clinical Response

In Trial PsA, SIMPONI ARIA treatment, compared with placebo, resulted in a significant improvement in signs and symptoms as demonstrated by the percentage of patients with an ACR 20 response at Week 14 (see Table 5). Similar ACR 20 responses at Week 24 were observed in patients with different PsA subtypes. ACR 20 responses observed in the SIMPONI ARIA-treated groups were similar in patients who were or were not receiving concomitant MTX.

Table 5: Trial PsA –Percentage of Patients with ACR Responses at Weeks 14 and 24
 | Placebo | SIMPONI ARIA | Difference from placebo (95% CI)
 | (N [N reflects randomized patients. Bold text indicates primary endpoint.] =239) | (N =241)
ACR 20 response
Week 14 | 22% | 75% | 53% [p<0.001] (46, 61)
Week 24 | 24% | 77% | 53% (45, 60)
ACR 50 response
Week 14 | 6.3% | 44% | 37% (30, 44)
Week 24 | 6.3% | 54% | 47% (40, 54)
ACR 70 response
Week 14 | 2.1% | 25% | 22% (17, 28)
Week 24 | 3.3% | 33% | 29% (23, 36)
Note: The analysis is based on the intent-to-treat population. Last observation carried forward was performed for partial missing data and non-responder imputation for completely missing data. Patients who discontinued treatment due to lack of efficacy were imputed as non-responders, as were patients who started prohibited medication, increased corticosteroids or MTX, or failed to achieve at least a 5% improvement in joint counts at Week 16 and received a concomitant medication intervention (corticosteroids, MTX or NSAIDs).

The percentage of patients achieving ACR20 responses by visit through Week 24 for Trial PsA is shown in Figure 2.

Figure 2: Trial PsA - Percentage of Patients Achieving ACR20 Response Through Week 24

The analysis is based on the intent-to-treat population. Last observation carried forward was performed for partial missing data and non-responder imputation for completely missing data. Patients who discontinued treatment due to lack of efficacy were imputed as non-responders, as were patients who started prohibited medication, increased corticosteroids or MTX, or failed to achieve at least a 5% improvement in joint counts at Week 16 and received a concomitant medication intervention (corticosteroids, MTX or NSAIDs).

Table 6 shows the improvement in the individual components of the ACR response criteria for the SIMPONI ARIA and placebo groups in Trial PsA.

Table 6: Trial PsA – Mean Changes in ACR Components at Week 14
 | Placebo N [N reflects randomized patients; actual number of patients evaluable for each endpoint may vary.] =239 |  | SIMPONI ARIA N =241
 | Baseline | Week 14 change from baseline | Baseline | Week 14 change from baseline
ACR Components
No. of Swollen Joints (0–66) | 14 | -2.9 | 14 | -11
Number of Tender Joints (0–68) | 26 | -4.2 | 25 | -15
Patient's assessment of Pain (0–100 mm) | 64 | -11 | 63 | -31
Patient Global Assessment (0–100 mm) | 63 | -11 | 65 | -32
Physician Global Assessment (0–100 mm) | 64 | -13 | 62 | -39
Disability Index (HAQ) (0–3) [Health Assessment Questionnaire-Disability Index.] | 1.3 | -0.13 | 1.3 | -0.60
hsCRP (mg/L) | 20 | -2.9 | 19 | -16
Note: All values are means.

Patients with enthesitis at baseline were evaluated for mean improvement using the Leeds Enthesitis Index (LEI) on a scale of 0–6. SIMPONI ARIA-treated patients showed a significantly greater improvement in enthesitis, with a mean reduction of 1.8 as compared with a mean reduction in placebo-treated patients of 0.8 at Week 14. Patients with dactylitis at baseline were evaluated for mean improvement on a scale of 0–60. SIMPONI ARIA-treated patients showed a significantly greater improvement, with a mean reduction of 7.8 compared with a mean reduction of 2.8 in placebo-treated patients at Week 14.

Radiographic Response

In Trial PsA, structural joint damage was assessed radiographically and expressed as a change from baseline at Week 24 in total modified vdH-S score and its components, the erosion score and JSN score. SIMPONI ARIA inhibited the progression of structural damage compared with placebo, as assessed by total modified vdH-S score as shown in Table 7.

Table 7: Trial PsA – Radiographic Change From Baseline at Week 24
 | Placebo N [N reflects randomized patients evaluable for radiographic assessment.] =237 | SIMPONI ARIA N =237 | Difference from placebo (95% CI)
 | Mean | Mean
Change Total Modified vdH-S Score | 2.0 | -0.4 | -2.3 (-2.9, -1.7)
Note: All values are means.

At Week 24, a greater proportion of patients in the SIMPONI ARIA group (72%) had no progression of structural damage (change in the total modified vdH-S score ≤ 0), compared to 43% of patients in the placebo group.

Physical Function and Responses

Improvement in physical function as assessed by the Health Assessment Questionnaire Disability Index (HAQ-DI) demonstrated that the proportion of patients who achieved clinically meaningful improvement of ≥ 0.3 in HAQ-DI score from baseline was greater in the SIMPONI ARIA-treated group compared to placebo at Week 14 (69% compared to 32%).

Other Health Related Outcomes

General health status was assessed by the 36-item Short Form Health Survey (SF-36). In Trial PsA, patients receiving SIMPONI ARIA demonstrated greater improvement from baseline compared with placebo in physical component summary, mental component summary scores and in all 8 domains of the SF-36.

Fatigue was assessed by the Functional Assessment of Chronic Illness Therapy-Fatigue score (FACIT-F) in Trial PsA. Treatment with SIMPONI ARIA resulted in improvement in fatigue as measured by FACIT-F.

Treatment of Pediatric Patients

The efficacy of SIMPONI ARIA in pediatric patients with PsA is based on the pharmacokinetic exposure and extrapolation of the established efficacy of SIMPONI ARIA in adult PsA patients in Trial PsA [see Use in Specific Populations (8.4), Clinical Pharmacology (12.3), Clinical Studies (14.4)].

14.3 Ankylosing Spondylitis

The efficacy and safety of SIMPONI ARIA were evaluated in a multicenter, randomized, double-blind, placebo-controlled trial (Trial AS, NCT02186873) in 208 patients ≥ 18 years of age with active ankylosing spondylitis (AS) and inadequate response or intolerance to NSAIDs. Patients had a diagnosis of definite AS for at least 3 months according to modified New York criteria. Patients had symptoms of active disease [Bath AS Disease Activity Index (BASDAI) ≥ 4, VAS for total back pain of ≥ 4, on scales of 0 to 10 cm (0 to 100 mm), and a hsCRP level of ≥ 0.3 mg/dL (3 mg/L)]. Patients were randomized to receive either SIMPONI ARIA 2 mg/kg (N=105) or placebo (N=103) as a 30-minute intravenous infusion at Weeks 0, 4 and 12. All patients on placebo received SIMPONI ARIA at Week 16, Week 20 and every 8 weeks thereafter through Week 52. Patients in the SIMPONI ARIA treatment group continued to receive SIMPONI ARIA infusions at Week 20 and every 8 weeks through Week 52. Patients were allowed to continue stable doses of concomitant MTX, SSZ, hydroxychloroquine (HCQ), low dose oral corticosteroids (equivalent to ≤ 10 mg of prednisone per day), and/or NSAIDs during the trial. The use of other DMARDs including cytotoxic agents or other biologics was prohibited.

The primary endpoint was the percentage of patients achieving an Assessment in Ankylosing Spondylitis (ASAS) 20 response at Week 16.

In Trial AS, the median duration of AS disease was 2.8 years, median duration of inflammatory back pain was 8 years, 90% were HLA-B27 positive, 8.2% had prior joint surgery or procedure, 5.8% had complete ankylosis of the spine, 14% had received prior therapy with one biologic TNF blocker (other than golimumab) and discontinued for reasons other than lack of efficacy within the first 16 weeks of treatment (primary failure), and 76% received at least one DMARD in the past. During the trial, the use of concomitant medications was NSAIDs (88%), SSZ (38%), corticosteroids (26%), MTX (18%), and HCQ (0.5%).

Clinical Response

In Trial AS, SIMPONI ARIA treatment, compared with placebo, resulted in a significant improvement in signs and symptoms as demonstrated by the percentage of patients with an ASAS 20 response at Week 16 (see Table 8).

Table 8: Trial AS – Percentage of ASAS Responders at Weeks 16
 | Placebo N [N reflects randomized patients. Bold text indicates primary endpoint.] =103 | SIMPONI ARIA N =105 | Treatment Difference (95% CI)
Responders
ASAS 20 | 26% | 73% | 47% [p<0.001] (35, 59)
ASAS 40 | 8.7% | 48% | 39% (28, 50)
Note: The analysis is based on the intent-to-treat population. Last observation carried forward was performed for partial missing data and non-responder imputation for completely missing data.

The percentage of patients achieving ASAS 20 responses by visit through Week 16 for Trial AS is shown in Figure 3.

Figure 3: Trial AS – Percentage of Patients Achieving an ASAS 20 Response Through Week 16

The analysis is based on the intent-to-treat population. Last observation carried forward was performed for partial missing data and non-responder imputation for completely missing data.

Table 9 shows the improvement in the components of the ASAS response criteria and other measures of disease activity for the SIMPONI ARIA and placebo groups in Trial AS.

Table 9: Trial AS – Mean Changes in ASAS 20 Components and Other Measures of Disease Activity at Week 16 [N reflects randomized patients; actual number of patients evaluable for each endpoint may vary.]
 | Placebo N =103 |  | SIMPONI ARIA N =105
 | Baseline | Week 16 change from baseline | Baseline | Week 16 change from baseline
ASAS 20 Response criteria
Patient Global Assessment of Disease Activity (0–100 mm) [Measured on a Visual Analog Scale (VAS) with 0= very well, 100=very poor] | 71 | -8.3 | 73 | -34
Total back pain (0–100 mm) [Measured on a Visual Analog Scale (VAS) with 0= no pain, 100=most severe pain] | 73 | -12 | 72 | -32
BASFI (0–10) [BASFI is Bath Ankylosing Spondylitis Functional Index.] | 6.1 | -0.5 | 6.3 | -2.4
Inflammation (0–10) [Inflammation is the mean of 2 morning stiffness self-assessments in the BASDAI.] | 7.4 | -1.1 | 7.3 | -3.6
BASDAI Score | 7.1 | -1.1 | 7.1 | -3.1
BASMI [Bath Ankylosing Spondylitis Metrology Index.] | 5.0 | -0.1 | 5.0 | -0.4
hsCRP (mg/L) | 19 | -2.3 | 20 | -17
Note: All values are means.

At Week 16, a greater percentage of patients treated with SIMPONI ARIA achieved a low level of disease activity (<2 [on a scale of 0 to 10 cm] in all four ASAS domains) compared with patients treated with placebo (16.2% vs. 3.9%).

Other Health-Related Outcomes

General health status was assessed by the 36-item Short Form Health Survey (SF-36). In Trial AS, patients receiving SIMPONI ARIA demonstrated greater improvement from baseline compared with placebo in physical component summary and mental component summary scores and in all 8 domains of the SF-36.

SIMPONI ARIA-treated patients showed significant improvement compared with placebo-treated patients in health related quality of life as assessed by the Ankylosing Spondylitis Quality of Life questionnaire (ASQoL).

14.4 Polyarticular Juvenile Idiopathic Arthritis (pJIA)

The efficacy of SIMPONI ARIA in pediatric patients with pJIA is based on the pharmacokinetic exposure and extrapolation of the established efficacy of SIMPONI ARIA in RA patients. Efficacy of SIMPONI ARIA was also assessed in a multicenter, open-label, single-arm study in 127 children (2 to < 18 years of age) with JIA with active polyarthritis despite treatment with MTX for at least 2 months (Trial pJIA, NCT02277444). The polyarticular JIA patient subtypes at study entry included: rheumatoid factor negative (43%), rheumatoid factor positive (35%), enthesitis-related arthritis (9%), oligoarticular extended (6%), juvenile psoriatic arthritis (4%), and systemic JIA without systemic manifestations (3%). All patients received SIMPONI ARIA 80 mg/m^2as an intravenous infusion at Week 0, 4, and every 8 weeks through Week 52. Patients continued stable doses of MTX weekly through Week 28; after Week 28, changes in MTX dose were permitted. Efficacy was assessed as supportive endpoints through Week 52. The efficacy was generally consistent with responses in patients with RA.

16 HOW SUPPLIED/STORAGE AND HANDLING

SIMPONI ARIA®(golimumab) Injection is a colorless to light yellow solution available in packs of 1 vial NDC 57894-350-01.

Vial

Each single-dose vial contains 50 mg of SIMPONI ARIA per 4 mL of solution.

Storage and Handling

Refrigerate SIMPONI ARIA at 36 ⁰F to 46 ⁰F (2 ⁰C to 8 ⁰C) and protect from light. Keep the product in the original carton to protect from light until the time of use. Do not freeze. Do not shake.

If needed, SIMPONI ARIA may be stored at room temperature up to 77 ºF (25 ºC) for a maximum single period of 30 days in the original carton to protect from light. Once SIMPONI ARIA has been stored at room temperature, do not return the product to the refrigerator. If not used within 30 days at room temperature, discard SIMPONI ARIA.

17 PATIENT COUNSELING INFORMATION

See FDA-approved patient labeling (Medication Guide).

Advise patients of the potential benefits and risks of SIMPONI ARIA. Instruct patients to read the Medication Guide before starting SIMPONI ARIA therapy and to read it each time the prescription is renewed.

Infections

Inform patients that SIMPONI ARIA may lower the ability of their immune system to fight infections. Instruct the patient of the importance of contacting their doctor if they develop any symptoms of infection, including tuberculosis, invasive fungal infections, and hepatitis B reactivation.

Malignancies

Patients should be counseled about the risk of lymphoma and other malignancies while receiving SIMPONI ARIA. Periodic skin examination is recommended for all patients, particularly those with risk factors for skin cancer.

Other Medical Conditions

Advise patients to report any signs of new or worsening medical conditions such as congestive heart failure, demyelinating disorders, autoimmune diseases, liver disease, cytopenias, or psoriasis.

Vaccinations

Inform patients that because SIMPONI ARIA may lower the ability of their immune system to fight infections, they should avoid live vaccines. Inform pregnant patients receiving SIMPONI ARIA that their infants should not receive live vaccines for 6 months following the last infusion of SIMPONI ARIA during pregnancy. Advise patients and infants of women who received SIMPONI ARIA during pregnancy to consult a physician before receiving any immunizations.

Manufactured by:
Janssen Biotech, Inc.
Horsham, PA 19044, USA
US License No. 1864
For patent information: www.janssenpatents.com

© 2017, 2020 Janssen Pharmaceutical Companies

MEDICATION GUIDE
SIMPONI ARIA®(SIM-po-nee AHR-ee-uh)
(golimumab)
injection, for intravenous use

What is the most important information I should know about SIMPONI ARIA?

SIMPONI ARIA is a medicine that affects your immune system. SIMPONI ARIA can lower the ability of your immune system to fight infections. Some people have serious infections while receiving SIMPONI ARIA, including tuberculosis (TB), and infections caused by bacteria, fungi, or viruses that spread throughout their body. Some people have died from these serious infections.

- Your doctor should test you for TB and hepatitis B before starting SIMPONI ARIA.
- Your doctor should monitor you closely for signs and symptoms of TB during treatment with SIMPONI ARIA.

You should not start receiving SIMPONI ARIA if you have any kind of infection unless your doctor tells you to.

Before receiving SIMPONI ARIA, tell your doctor if you:

- think you have an infection or have symptoms of an infection such as:

- fever, sweat, or chills
- muscle aches
- cough
- shortness of breath
- blood in phlegm
- weight loss

- warm, red, or painful skin or sores on your body
- diarrhea or stomach pain
- burning when you urinate or urinate more often than normal
- feel very tired

- are being treated for an infection.
- get a lot of infections or have infections that keep coming back.
- have diabetes, HIV, or a weak immune system. People with these conditions have a higher chance for infections.
- have TB, or have been in close contact with someone with TB.
- live, have lived, or traveled to certain parts of the country (such as the Ohio and Mississippi River valleys and the Southwest) where there is an increased chance for getting certain kinds of fungal infections (histoplasmosis, coccidioidomycosis, blastomycosis). These infections may happen or become more severe if you use SIMPONI ARIA. Ask your doctor if you do not know if you have lived in an area where these infections are common.
- have or have had hepatitis B.
- use the medicine ORENCIA (abatacept), KINERET (anakinra), ACTEMRA (tocilizumab) or RITUXAN (rituximab).

After receiving SIMPONI ARIA, call your doctor right away if you have any symptoms of an infection. SIMPONI ARIA can make you more likely to get infections or make worse any infection that you have.

Cancer

- For children and adults receiving Tumor Necrosis Factor (TNF)-blocker medicines, including SIMPONI ARIA, the chances of getting cancer may increase.
- There have been cases of unusual cancers in children and teenage patients receiving TNF-blocking agents.
- People with inflammatory diseases, including rheumatoid arthritis (RA), especially those with very active disease, may be more likely to get lymphoma.
- Some people receiving TNF-blockers, like SIMPONI ARIA, developed a rare type of cancer called hepatosplenic T-cell lymphoma. This type of cancer often results in death. Most of these people were male teenagers or young men. Also, most people were being treated for Crohn's disease or ulcerative colitis with a TNF blocker and another medicine called azathioprine or 6-mercaptopurine, (6-MP).
- Some people treated with SIMPONI ARIA developed skin cancer. If any changes in the appearance of your skin or growths on your skin occur during or after your treatment with SIMPONI ARIA, tell your doctor.
- You should see your doctor periodically for skin examinations, especially if you have a history of skin cancer.

What is SIMPONI ARIA?

SIMPONI ARIA is a prescription medicine called a TNF-blocker. SIMPONI ARIA is used to treat:

- Adults with the medicine methotrexate (MTX) to treat moderately to severely active RA.
- Active psoriatic arthritis (PsA) in people 2 years of age and older.
- Adults with active ankylosing spondylitis (AS).
- Active polyarticular juvenile idiopathic arthritis (pJIA) in people 2 years of age and older.

It is not known if SIMPONI ARIA is safe and effective in children with PsA and pJIA under 2 years of age or in children with conditions other than PsA and pJIA.

What should I tell my doctor before starting treatment with SIMPONI ARIA?

See " What is the most important information I should know about SIMPONI ARIA?".

Before starting SIMPONI ARIA, tell your doctor about all your medical conditions, including if you:

- have an infection.
- have or have had lymphoma or any other type of cancer.
- have or have had heart failure.
- have or have had a condition that affects your nervous system, such as multiple sclerosis or Guillain-Barré syndrome.
- have a skin problem called psoriasis.
- have recently received or are scheduled to receive a vaccine. People receiving SIMPONI ARIA should not receive live vaccines or treatment with a weakened bacteria (such as BCG for bladder cancer). People receiving SIMPONI ARIA can receive non-live vaccines.
- have a baby and you were receiving SIMPONI ARIA during your pregnancy. Tell your baby's doctor before your baby receives any vaccine. Your baby may have an increased chance of getting an infection for up to 6 months after birth.
- are pregnant or plan to become pregnant. It is not known if SIMPONI ARIA will harm your unborn baby.
- are breastfeeding or plan to breastfeed. It is not known if SIMPONI ARIA passes into your breast milk. You and your doctor should decide if you will receive SIMPONI ARIA or breastfeed.

Tell your doctor about all the medicines you take, including prescription and over-the-counter medicines, vitamins, and herbal supplements.

Especially, tell your doctor if you:

- use ORENCIA (abatacept) or KINERET (anakinra). You should not receive SIMPONI ARIA while you are also receiving ORENCIA (abatacept) or KINERET (anakinra).
- use other TNF-blocker medicines, including REMICADE (infliximab), HUMIRA (adalimumab), ENBREL (etanercept), or CIMZIA (certolizumab pegol).
- receive RITUXAN (rituximab) or ACTEMRA (tocilizumab).

Ask your doctor or pharmacist for a list of these medicines if you are not sure.

Keep a list of all your medicines with you to show your doctor and pharmacist each time you get a new medicine.

How should I receive SIMPONI ARIA?

- SIMPONI ARIA is prepared and given by a healthcare provider through a needle placed in your vein (infusion). The infusion is usually given in your arm and should take 30 minutes.
- Your doctor will decide how much SIMPONI ARIA you will receive. Your usual schedule for receiving SIMPONI ARIA after your first treatment should be:

- 4 weeks after your first treatment
- every 8 weeks after that

- If you miss an appointment to receive SIMPONI ARIA, make another appointment as soon as possible.

What are the possible side effects of SIMPONI ARIA?

SIMPONI ARIA can cause serious side effects, including:

See " What is the most important information I should know about SIMPONI ARIA?"
Serious Infections.

- Some patients have an increased chance of getting serious infections while receiving SIMPONI ARIA. These serious infections include TB and infections caused by viruses, fungi, or bacteria that have spread throughout the body. Some patients die from these infections. If you get an infection while receiving treatment with SIMPONI ARIA your doctor will treat your infection and may need to stop your SIMPONI ARIA treatment. Tell your doctor right away if you have any of the following signs of an infection while receiving or after receiving SIMPONI ARIA:

- a fever
- feel very tired
- have a cough

- have flu-like symptoms
- warm, red, or painful skin

- Your doctor will examine you for TB and perform a test to see if you have TB. If your doctor feels that you are at risk for TB, you may be treated with medicine for TB before you begin treatment with SIMPONI ARIA and during treatment with SIMPONI ARIA. Even if your TB test is negative your doctor should carefully monitor you for TB infections while you are receiving SIMPONI ARIA. People who had a negative TB skin test before receiving SIMPONI ARIA have developed active TB. Tell your doctor if you have any of the following symptoms while receiving or after receiving SIMPONI ARIA:

- cough that does not go away
- low grade fever

- weight loss
- loss of body fat and muscle (wasting)

Hepatitis B infection in people who carry the virus in their blood.If you are a carrier of the hepatitis B virus (a virus that affects the liver), the virus can become active while you use SIMPONI ARIA. Your doctor should do blood tests before you start treatment with SIMPONI ARIA and while you are receiving SIMPONI ARIA.

- Tell your doctor if you have any of the following symptoms of a possible hepatitis B infection:

- feel very tired
- dark urine
- skin or eyes look yellow
- little or no appetite
- vomiting
- muscle aches

- clay-colored bowel movements
- fevers
- chills
- stomach discomfort
- skin rash

Heart failure, including new heart failure or worsening of heart failure that you already have can happen in people who use TNF-blocker medicines, including SIMPONI ARIA.If you develop new or worsening heart failure with SIMPONI ARIA, you may need to be treated in a hospital, and it may result in death.

- If you have heart failure before starting SIMPONI ARIA, your condition should be watched closely during treatment with SIMPONI ARIA.
- Call your doctor right away if you get new or worsening symptoms of heart failure during treatment with SIMPONI ARIA (such as shortness of breath or swelling of your lower legs or feet, or sudden weight gain).

Nervous System Problems.Rarely, people receiving TNF-blocker medicines, including SIMPONI ARIA, have nervous system problems such as multiple sclerosis or Guillain-Barré syndrome. Tell your doctor right away if you get any of these symptoms:

- vision changes
- weakness in your arms or legs

- numbness or tingling in any part of your body

Immune System Problems.Rarely, people receiving TNF-blocker medicines have developed symptoms that are like the symptoms of lupus. Tell your doctor if you have any of these symptoms:

- a rash on your cheeks or other parts of the body
- sensitivity to the sun
- new joint or muscle pains

- becoming very tired
- chest pain or shortness of breath
- swelling of the feet, ankles, or legs

Liver Problems.Liver problems can happen in people who receive TNF-blocker medicines, including SIMPONI ARIA. These problems can lead to liver failure and death. Call your doctor right away if you have any of these symptoms:

- feel very tired
- skin or eyes look yellow

- poor appetite or vomiting
- pain on the right side of your stomach (abdomen)

Blood Problems.Low blood counts have been seen with SIMPONI ARIA. Your body may not make enough blood cells that help fight infections or help stop bleeding. Symptoms include fever, bruising or bleeding easily, or looking pale. Your doctor will check your blood counts before and during treatment with SIMPONI ARIA.

Allergic Reactions.Allergic reactions can happen in people who receive TNF-blocker medicines, including SIMPONI ARIA. Some reactions may be serious and can be life-threatening. Some of these reactions can happen after receiving your first dose of SIMPONI ARIA. Call your doctor right away if you have any of these symptoms of an allergic reaction:

- hives
- swollen face

- breathing trouble
- chest pain

The most common side effects of SIMPONI ARIA include:

- upper respiratory infection (runny nose, sore throat, and hoarseness or laryngitis)
- abnormal liver tests
- decreased blood cells that fight infection
- viral infections, such as flu and cold sores in the mouth
- bronchitis
- high blood pressure
- rash

These are not all of the possible side effects of SIMPONI ARIA.

Tell your doctor about any side effect that bothers you or does not go away. Call your doctor for medical advice about side effects. You may report side effects to FDA at 1-800-FDA-1088.

General information about the safe and effective use of SIMPONI ARIA.

Medicines are sometimes prescribed for purposes other than those listed in a Medication Guide.

You can ask your doctor or pharmacist for information about SIMPONI ARIA that is written for health professionals.

What are the ingredients in SIMPONI ARIA?

Active ingredient: golimumab.

Inactive ingredients: L-histidine, L-histidine monohydrochloride monohydrate, polysorbate 80, sorbitol, and water for injection. SIMPONI ARIA is preservative-free and is not made with natural rubber latex.

Manufactured by: Janssen Biotech, Inc. Horsham, PA 19044, USA US License No. 1864 For patent information: www.janssenpatents.com
© 2017, 2020 Janssen Pharmaceutical Companies

For more information go to www.SIMPONIARIA.com or call 1-800-JANSSEN (1-800-526-7736).

This Medication Guide has been approved by the U.S. Food and Drug Administration

Revised: 9/2020

PRINCIPAL DISPLAY PANEL - 4 mL Vial Carton

NDC 57894-350-01

Simponi ARIA®
golimumab

50 mg/4 mL
(12.5 mg/mL)

For intravenous infusion

Single-dose vial.
Discard unused portion.
Rx Only

Provide the enclosed Medication
Guide to each patient.